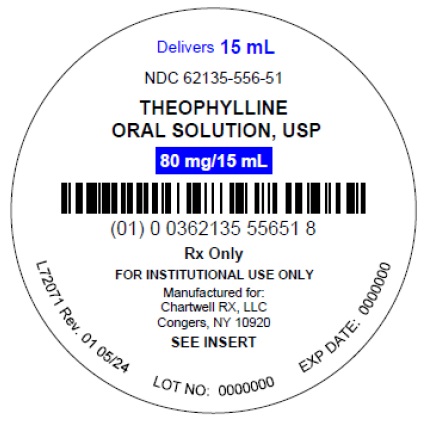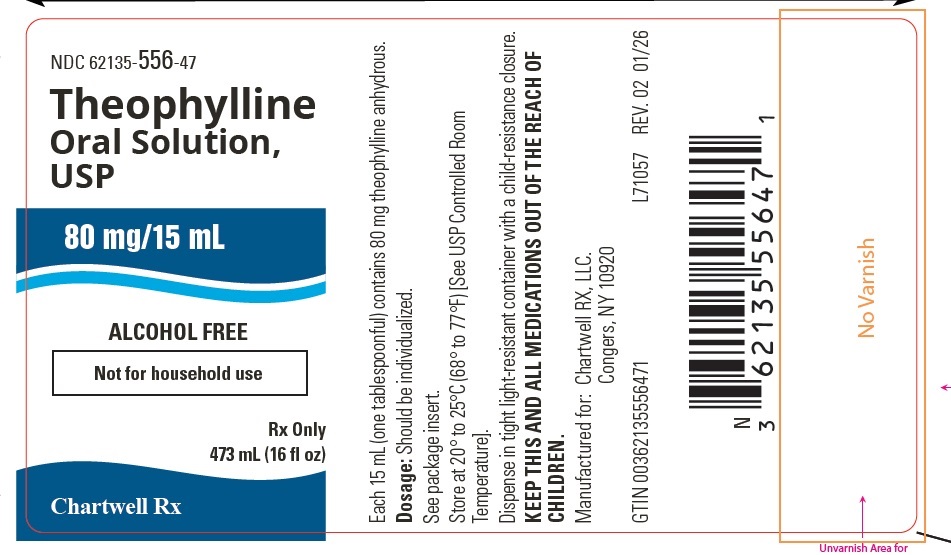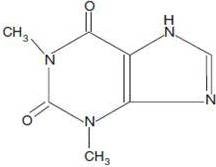 DRUG LABEL: Theophylline
NDC: 62135-556 | Form: SOLUTION
Manufacturer: Chartwell RX, LLC
Category: prescription | Type: HUMAN PRESCRIPTION DRUG LABEL
Date: 20260206

ACTIVE INGREDIENTS: THEOPHYLLINE ANHYDROUS 80 mg/15 mL
INACTIVE INGREDIENTS: ANHYDROUS CITRIC ACID; SACCHARIN SODIUM; SODIUM BENZOATE; GLYCERIN; PROPYLENE GLYCOL; FD&C RED NO. 40; WATER

THEOPHYLLINE ORAL SOLUTION, USP

DESCRIPTION

Theophylline is structurally classified as a methylxanthine. It occurs as a white, odorless, crystalline powder with a bitter taste. Anhydrous theophylline has the chemical name 1H-Purine- 2,6-dione, 3,7-dihydro-1 ,3 -dimethyl-, and is represented by the following structural formula:

The molecular formula of anhydrous theophylline is C7H8N4O2with a molecular weight of 180.17.Theophylline Oral Solution, USP is available as a clear red color liquid with a fruit flavor intended for oral administration, containing 80 mg of theophylline anhydrous in each 15 mL (tablespoonful).Theophylline Oral Solution, USP also contains the following inactive ingredients: citric acid, sodium saccharin, sodium benzoate, glycerin, propylene glycol, FD&C Red #40, natural and artificial fruity flavor and purified water. Theophylline Oral Solution, USP has a pH of 4.3 - 4.7

CLINICAL PHARMACOLOGY

Mechanism of Action:

Theophylline has two distinct actions in the airways of patients with reversible obstruction; smooth muscle relaxation (i.e., bronchodilation) and suppression of the response of the airways to stimuli (i.e., non-bronchodilator prophylactic effects). While the mechanisms of action of theophylline are not known with certainty, studies in animals suggest that bronchodilatation is mediated by the inhibition of two isozymes of phosphodiesterase (PDE III and, to a lesser extent, PDE IV) while non-bronchodilator prophylactic actions are probably mediated through one or more different molecular mechanisms, that do not involve inhibition of PDE III or antagonism of adenosine receptors. Some of the adverse effects associated with theophylline appear to be mediated by inhibition of PDE III (e.g., hypotension, tachycardia, headache, and emesis) and adenosine receptor antagonism (e.g., alterations in cerebral blood flow).

Theophylline increases the force of contraction of diaphragmatic muscles. This action appears to be due to enhancement of calcium uptake through an adenosine-mediated channel.

Serum Concentration-Effect Relationship:

Bronchodilation occurs over the serum theophylline concentration range of 5-20 mcg/mL. Clinically important improvement in symptom control has been found in most studies to require peak serum theophylline concentrations >10 mcg/mL, but patients with mild disease may benefit from lower concentrations. At serum theophylline concentrations >20mcg/mL, both the frequency and severity of adverse reactions increase. In general, maintaining peak serum theophylline concentrations between 10 and 15 mcg/mL will achieve most of the drug's potential therapeutic benefit while minimizing the risk of serious adverse events.

Pharmacokinetics:
Overview
Theophylline is rapidly and completely absorbed after oral administration in solution or immediate-release solid oral dosage form. Theophylline does not undergo any appreciable pre-systemic elimination, distributes freely into fat-free tissues and is extensively metabolized in the liver.

The pharmacokinetics of theophylline vary widely among similar patients and cannot be predicted by age, sex, body weight or other demographic characteristics. In addition, certain concurrent illnesses and alterations in normal physiology (see Table I) and co-administration of other drugs (see Table II) can significantly alter the pharmacokinetic characteristics of theophylline. Within-subject variability in metabolism has also been reported in some studies, especially in acutely ill patients. It is, therefore, recommended that serum theophylline concentrations be measured frequently in acutely ill patients (e.g., at 24-hour intervals) and periodically in patients receiving long-term therapy, e.g., at 6-12 month intervals. More frequent measurements should be made in the presence of any condition that may significantly alter theophylline clearance (see PRECAUTIONS, Laboratory tests).

Table I. Mean and range of total body clearance and half-life of theophylline related to age and altered physiological states.

Population characteristics | Total body clearance* mean (range)†† (mL/kg/min) | Half-life mean (range)†† (hr)
Age
Premature neonates
postnatal age 3-15 days | 0.29 (0.09-0.49) | 30 (17-43)
postnatal age 25-57 days | 0.64 (0.04-1.2) | 20 (9.4-30.6)
Term infants
postnatal age 1-2 days | NR† | 25.7 (25-26.5)
postnatal age 3-30 weeks | NR† | 11 (6-29)
Children
1-4 years | 1.7 (0.5-2.9) | 3.4 (1.2-5.6)
4-12 years | 1.6 (0.8-2.4) | NR†
13-15 years | 0.9 (0.48-1.3) | NR†
16-17 years | 1.4 (0.2-2.6) | 3.7 (1.5-5.9)
Adults (16-60 years)
otherwise healthy
non-smoking asthmatics | 0.65 (0.27-1.03) | 8.7 (6.1-12.8)
Elderly (>60 years)
non-smokers with normal cardiac, liver, and renal function | 0.41 (0.21-0.61) | 9.8 (1.6-18)
Concurrent illness or altered physiological state
Acute pulmonary edema | 0.33** (0.07-2.45) | 19** (3.1-82)
COPD->60 years, stable non-smoker >1 year | 0.54 (0.44-0.64) | 11 (9.4-12.6)
COPD with cor pulmonale | 0.48 (0.08-0.88) | NR†
Cystic fibrosis (14-28 years) | 1.25 (0.31-2.2) | 6.0 (1.8-10.2)
Fever associated with acute viral respiratory illness (children 9-15 years) | NR† | 7.0 (1.0-13)
Liver disease - cirrhosis | 0.31** (0.1-0.7) | 32** (10-56)
acute hepatitis | 0.35 (0.25-0.45) | 19.2 (16.6-21.8)
cholestasis | 0.65 (0.25-1.45) | 14.4 (5.7-31.8)
Pregnancy - 1st trimester | NR† | 8.5 (3.1-13.9)
2nd trimester | NR† | 8.8 (3.8-13.8)
3rd trimester | NR† | 13.0 (8.4-17.6)
Sepsis with multi-organ failure | 0.47 (0.19-1.9) | 18.8 (6.3-24.1)
Thyroid disease - hypothyroid | 0.38 (0.13-0.57) | 11.6 (8.2-25)
hyperthyroid | 0.8 (0.68-0.97) | 4.5 (3.7-5.6)

For various North American patient populations from literature reports. Different rates of elimination and consequent dosage requirements have been observed among other peoples.

*Clearance represents the volume of blood completely cleared of theophylline by the liver in one minute. Values listed were generally determined at serum theophylline concentrations <20 mcg/mL; clearance may decrease and half-life may increase at higher serum concentrations due to non-linear pharmacokinetics.

††Reported range or estimated range (mean ± 2 SD) where actual range not reported.

†NR = not reported or not reported in a comparable format.

**Median
Note: In addition to the factors listed above, theophylline clearance is increased and half-life decreased by low carbohydrate/high protein diets, parenteral nutrition, and daily consumption of charcoal-broiled beef. A high carbohydrate/low protein diet can decrease the clearance and prolong the half-life of theophylline.

AbsorptionTheophylline is rapidly and completely absorbed after oral administration in solution or immediate-release solid oral dosage form. After a single dose of 5 mg/kg in adults, a mean peak serum concentration of about 10 mcg/mL (range 5-15 mcg/mL) can be expected 1-2 hr after the dose. Co-administration of theophylline with food or antacids does not cause clinically significant changes in the absorption of theophylline from immediate-release dosage forms.

DistributionOnce theophylline enters the systemic circulation, about 40% is bound to plasma protein, primarily albumin. Unbound theophylline distributes throughout body water, but distributes poorly into body fat. The apparent volume of distribution of theophylline is approximately 0.45 L/kg (range 0.3-0.7 L/kg) based on ideal body weight. Theophylline passes freely across the placenta, into breast milk and into the cerebrospinal fluid (CSF). Saliva theophylline concentrations approximate unbound serum concentrations, but are not reliable for routine or therapeutic monitoring unless special techniques are used. An increase in the volume of distribution of theophylline, primarily due to reduction in plasma protein binding, occurs in premature neonates, patients with hepatic cirrhosis, uncorrected acidemia, the elderly and in women during the third trimester of pregnancy. In such cases, the patient may show signs of toxicity at total (bound + unbound) serum concentrations of theophylline in the therapeutic range (10-20 mcg/mL) due to elevated concentrations of the pharmacologically active unbound drug. Similarly, a patient with decreased theophylline binding may have a subtherapeutic total drug concentration while the pharmacologically active unbound concentration is in the therapeutic range. If only total serum theophylline concentration is measured, this may lead to an unnecessary and potentially dangerous dose increase. In patients with reduced protein binding, measurement of unbound serum theophylline concentration provides a more reliable means of dosage adjustment than measurement of total serum theophylline concentration. Generally, concentrations of unbound theophylline should be maintained in the range of 6-12 mcg/mL.

MetabolismFollowing oral dosing, theophylline does not undergo any measurable first-pass elimination. In adults and children beyond one year of age, approximately 90% of the dose is metabolized in the liver. Biotransformation takes place through demethylation to 1-methylxanthine and 3-methylxanthine and hydroxylation to 1 ,3-dimethyluric acid. 1 -methylxanthine is further hydroxylated, by xanthine oxidase, to 1-methyluric acid. About 6% of a theophylline dose is N-methylated to caffeine. Theophylline demethylation to 3-methylxanthine is catalyzed by cytochrome P-450 1A2, while cytochromes P-450 2E1 and P-450 3A3 catalyze the hydroxylation to 1,3-dimethyluric acid. Demethylation to 1-methylxanthine appears to be catalyzed either by cytochrome P-450 1A2 or a closely related cytochrome. In neonates, the N-demethylation pathway is absent while the function of the hydroxylation pathway is markedly deficient. The activity of these pathways slowly increases to maximal levels by one year of age.

Caffeine and 3-methylxanthine are the only theophylline metabolites with pharmacologic activity. 3-methylxanthine has approximately one tenth the pharmacologic activity of theophylline and serum concentrations in adults with normal renal function are <1 mcg/mL. In patients with end-stage renal disease, 3-methylxanthine may accumulate to concentrations that approximate the unmetabolized theophylline concentration. Caffeine concentrations are usually undetectable in adults regardless of renal function. In neonates, caffeine may accumulate to concentrations that approximate the unmetabolized theophylline concentration and thus, exert a pharmacologic effect.

Both the N-demethylation and hydroxylation pathways of theophylline biotransformation are capacity-limited. Due to the wide intersubject variability of the rate of theophylline metabolism, non-linearity of elimination may begin in some patients at serum theophylline concentrations <10 mcg/mL. Since this non-linearity results in more than proportional changes in serum theophylline concentrations with changes in dose, it is advisable to make increases or decreases in dose in small increments in order to achieve desired changes in serum theophylline concentrations (see DOSAGE AND ADMINISTRATION, Table VI). Accurate prediction of dose-dependency of theophylline metabolism in patients a prioriis not possible, but patients with very high initial clearance rates (i.e., low steady state serum theophylline concentrations at above average doses) have the greatest likelihood of experiencing large changes in serum theophylline concentration in response to dosage changes.

ExcretionIn neonates, approximately 50% of the theophylline dose is excreted unchanged in the urine. Beyond the first three months of life, approximately 10% of the theophylline dose is excreted unchanged in the urine. The remainder is excreted in the urine mainly as 1 ,3-dimethyluric acid (35-40%), 1-methyluric acid (20-25%) and 3-methylxanthine (15-20%). Since little theophylline is excreted unchanged in the urine and since active metabolites of theophylline (i.e., caffeine, 3-methylxanthine) do not accumulate to clinically significant levels even in the face of end-stage renal disease, no dosage adjustment for renal insufficiency is necessary in adults and children >3 months of age. In contrast, the large fraction of the theophylline dose excreted in the urine as unchanged theophylline and caffeine in neonates requires careful attention to dose reduction and frequent monitoring of serum theophylline concentrations in neonates with reduced renal function (See WARNINGS).

Serum Concentrations at Steady StateAfter multiple doses of theophylline, steady state is reached in 30-65 hours (average 40 hours) in adults. At steady state, on a dosage regimen with 6-hour intervals, the expected mean trough concentration is approximately 60% of the mean peak concentration, assuming a mean theophylline half-life of 8 hours. The difference between peak and trough concentrations is larger in patients with more rapid theophylline clearance. In patients with high theophylline clearance and half-lives of about 4-5 hours, such as children age 1 to 9 years, the trough serum theophylline concentration may be only 30% of peak with a 6-hour dosing interval. In these patients a slow release formulation would allow a longer dosing interval (8-12 hours) with a smaller peak/trough difference.

Special Populations

(See Table I for mean clearance and half-life values)

GeriatricThe clearance of theophylline is decreased by an average of 30% in healthy elderly adults (> 60 yrs) compared to healthy young adults. Careful attention to dose reduction and frequent monitoring of serum theophylline concentrations are required in elderly patients (see WARNINGS).

PediatricsThe clearance of theophylline is very low in neonates (see WARNINGS). Theophylline clearance reaches maximal values by one year of age, remains relatively constant until about 9 years of age and then slowly decreases by approximately 50% to adult values at about age 16. Renal excretion of unchanged theophylline in neonates amounts to about 50% of the dose, compared to about 10% in children older than three months and in adults. Careful attention to dosage selection and monitoring of serum theophylline concentrations are required in pediatric patients (see WARNINGS and DOSAGE AND ADMINISTRATION).

GenderGender differences in theophylline clearance are relatively small and unlikely to be of clinical significance. Significant reduction in theophylline clearance, however, has been reported in women on the 20th day of the menstrual cycle and during the third trimester of pregnancy.

RacePharmacokinetic differences in theophylline clearance due to race have not been studied.

Renal InsufficiencyOnly a small fraction, e.g., about 10%, of the administered theophylline dose is excreted unchanged in the urine of children greater than three months of age and adults. Since little theophylline is excreted unchanged in the urine and since active metabolites of theophylline (i.e., caffeine, 3-methylxanthine) do not accumulate to clinically significant levels even in the face of end-stage renal disease, no dosage adjustment for renal insufficiency is necessary in adults and children >3 months of age. In contrast, approximately 50% of the administered theophylline dose is excreted unchanged in the urine in neonates. Careful attention to dose reduction and frequent monitoring of serum theophylline concentrations are required in neonates with decreased renal function (see WARNINGS).

Hepatic InsufficiencyTheophylline clearance is decreased by 50% or more in patients with hepatic insufficiency (e.g., cirrhosis, acute hepatitis, cholestasis). Careful attention to dose reduction and frequent monitoring of serum theophylline concentrations are required in patients with reduced hepatic function (see WARNINGS).

Congestive Heart Failure (CHF)Theophylline clearance is decreased by 50% or more in patients with CHF. The extent of reduction in theophylline clearance in patients with CHF appears to be directly correlated to the severity of the cardiac disease. Since theophylline clearance is independent of liver blood flow, the reduction in clearance appears to be due to impaired hepatocyte function rather than reduced perfusion. Careful attention to dose reduction and frequent monitoring of serum theophylline concentrations are required in patients with CHF (see WARNINGS).

SmokersTobacco and marijuana smoking appears to increase the clearance of theophylline by induction of metabolic pathways. Theophylline clearance has been shown to increase by approximately 50% in young adult tobacco smokers and by approximately 80% in elderly tobacco smokers compared to non-smoking subjects. Passive smoke exposure has also been shown to increase theophylline clearance by up to 50%. Abstinence from tobacco smoking for one week causes a reduction of approximately 40% in theophylline clearance. Careful attention to dose reduction and frequent monitoring of serum theophylline concentrations are required in patients who stop smoking (see WARNINGS). Use of nicotine gum has been shown to have no effect on theophylline clearance.

FeverFever, regardless of its underlying cause, can decrease the clearance of theophylline. The magnitude and duration of the fever appear to be directly correlated to the degree of decrease of theophylline clearance. Precise data are lacking, but a temperature of 39˚C (102˚F) for at least 24 hours is probably required to produce a clinically significant increase in serum theophylline concentrations. Children with rapid rates of theophylline clearance (i.e., those who require a dose that is substantially larger than average [e.g., >22 mg/kg/day] to achieve a therapeutic peak serum theophylline concentration when afebrile) may be at greater risk of toxic effects from decreased clearance during sustained fever. Careful attention to dose reduction and frequent monitoring of serum theophylline concentrations are required in patients with sustained fever (see WARNINGS).

Miscellaneous

Other factors associated with decreased theophylline clearance include the third trimester of pregnancy, sepsis with multiple organ failure, and hypothyroidism. Careful attention to dose reduction and frequent monitoring of serum theophylline concentrations are required in patients with any of these conditions (see WARNINGS). Other factors associated with increased theophylline clearance include hyperthyroidism and cystic fibrosis.

Clinical Studies:

In patients with chronic asthma, including patients with severe asthma requiring inhaled corticosteroids or alternate-day oral corticosteroids, many clinical studies have shown that theophylline decreases the frequency and severity of symptoms, including nocturnal exacerbations, and decreases the “as needed” use of inhaled beta-2 agonists. Theophylline has also been shown to reduce the need for short courses of daily oral prednisone to relieve exacerbations of airway obstruction that are unresponsive to bronchodilators in asthmatics.

In patients with chronic obstructive pulmonary disease (COPD), clinical studies have shown that theophylline decreases dyspnea, air trapping, the work of breathing, and improves contractility of diaphragmatic muscles with little or no improvement in pulmonary function measurements.

INDICATIONS AND USAGE

Theophylline is indicated for the treatment of the symptoms and reversible airflow obstruction associated with chronic asthma and other chronic lung diseases, e.g., emphysema and chronic bronchitis.

CONTRAINDICATIONS

Theophylline Oral Solution is contraindicated in patients with a history of hypersensitivity to theophylline or other components in the product.

WARNINGS

Concurrent Illness:

Theophylline should be used with extreme caution in patients with the following clinical conditions due to the increased risk of exacerbation of the concurrent condition:

Active peptic ulcer disease

Seizure disorders

Cardiac arrhythmias (not including bradyarrhythmias)

Conditions That Reduce Theophylline Clearance:

There are several readily identifiable causes of reduced theophylline clearance. If the total daily dose is not appropriately reduced in the presence of these risk factors, severe and potentially fatal theophylline toxicity can occur.Careful consideration must be given to the benefits and risks of theophylline use and the need for more intensive motoring of serum theophylline concentrations in patients with the following risk factors:
Age

Neonates (term and premature)
Children <1 year
Elderly (>60 years)

Concurrent Diseases

Acute pulmonary edema
Congestive heart failure
Cor pulmonale
Fever; ≥102°F for 24 hours or more; or lesser temperature elevations for longer periods
Hypothyroidism
Liver disease; cirrhosis, acute hepatitis
Reduced renal function in infants <3 months of age
Sepsis with multi-organ failure
Shock

Cessation of Smoking

Drug InteractionsAdding a drug that inhibits theophylline metabolism (e.g., cimetidine, erythromycin, tacrine) or stopping a concurrently administered drug that enhances theophylline metabolism (e.g., carbamazepine, rifampin). (see PRECAUTIONS, Drug Interactions, Table II).

When Signs or Symptoms of Theophylline Toxicity Are Present:

Whenever a patient receiving theophylline develops nausea or vomiting, particularly repetitive vomiting or other signs or symptoms consistent with theophylline toxicity (even if another cause may be suspected), additional doses of theophylline should be withheld and a serum theophylline concentration measured immediately.Patients should be instructed not to continue any dosage that causes adverse effects and to withhold subsequent doses until the symptoms have resolved, at which time the clinician may instruct the patient to resume the drug at a lower dosage (see DOSAGE AND ADMINISTRATION, Dosing Guidelines, Table VI).

Dosage Increases:

Increases in the dose of theophylline should not be made in response to an acute exacerbation of symptoms of chronic lung disease since theophylline provides little added benefit to inhaled beta2-selective agonists and systemically administered corticosteroids in this circumstance and increases the risk of adverse effects. A peaksteady state serum theophylline concentration should be measured before increasing the dose in response to persistent chronic symptoms to ascertain whether an increase in dose is safe. Before increasing the theophylline dose on the basis of a low serum concentration, the clinician should consider whether the blood sample was obtained at an appropriate time in relationship to the dose and whether the patient has adhered to the prescribed regimen (see PRECAUTIONS, Laboratory Tests).

As the rate of theophylline clearance may be dose-dependent (i.e., steady-state serum concentrations may increase disproportionately to the increase in dose), an increase in dose based upon a sub-therapeutic serum concentration measurement should be conservative. In general, limiting dose increases to about 25% of the previous total daily dose will reduce the risk of unintended excessive increases in serum theophylline concentration (see DOSAGE AND ADMINISTRATION, Table VI).

PRECAUTIONS

General:

Careful consideration of the various interacting drugs and physiologic conditions that can alter theophylline clearance and require dosage adjustment should occur prior to initiation of theophylline therapy, prior to increases in theophylline dose, and during follow up (see WARNINGS). The dose of theophylline selected for initiation of therapy should be low and, if tolerated, increased slowly over a period of a week or longer with the final dose guided by monitoring serum theophylline concentrations and the patient's clinical response (see DOSAGE AND ADMINISTRATION, Table V).

Monitoring Serum Theophylline Concentrations:

Serum theophylline concentration measurements are readily available and should be used to determine whether the dosage is appropriate. Specifically, the serum theophylline concentration should be measured as follows:

1. When initiating therapy to guide final dosage adjustment after titration.
2. Before making a dose increase to determine whether the serum concentration is sub-therapeutic in a patient who continues to be symptomatic.
3. Whenever signs or symptoms of theophylline toxicity are present.
4. Whenever there is a new illness, worsening of a chronic illness or a change in the patient's treatment regimen that may alter theophylline clearance (e.g., fever >102°F sustained for 24 hours, hepatitis, or drugs listed in Table II are added or discontinued).

To guide a dose increase, the blood sample should be obtained at the time of the expected peak serum theophylline concentration; 1-2 hours after a dose at steady-state. For most patients, steady-state will be reached after 3 days of dosing when no doses have been missed, no extra doses have been added, and none of the doses have been taken at unequal intervals. A trough concentration (i.e., at the end of the dosing interval) provides no additional useful information and may lead to an inappropriate dose increase since the peak serum theophylline concentration can be two or more times greater than the trough concentration with an immediate-release formulation. If the serum sample is drawn more than two hours after the dose, the results must be interpreted with caution since the concentration may not be reflective of the peak concentration. In contrast, when signs or symptoms of theophylline toxicity are present, the serum sample should be obtained as soon as possible, analyzed immediately, and the result reported to the clinician without delay. In patients in whom decreased serum protein binding is suspected (e.g., cirrhosis, women during the third trimester of pregnancy), the concentration of unbound theophylline should be measured and the dosage adjusted to achieve an unbound concentration of 6-12 mcg/mL.

Saliva concentrations of theophylline cannot be used reliably to adjust dosage without special techniques.

Effects on Laboratory Tests:

As a result of its pharmacological effects, theophylline at serum concentrations within the 10-20 mcg/mL range modestly increases plasma glucose (from a mean of 88 mg% to 98 mg%), uric acid (from a mean of 4 mg/dl to 6 mg/dl), free fatty acids (from a mean of 451 μeq/l to 800 μeq/l), total cholesterol (from a mean of 140 vs 160 mg/dl), HDL (from a mean of 36 to 50 mg/dl), HDL/LDL ratio (from a mean of 0.5 to 0.7), and urinary free cortisol excretion (from a mean of 44 to 63 mcg/24 hr). Theophylline at serum concentrations within the 10-20 mcg/mL range may also transiently decrease serum concentrations of triiodothyronine (144 before, 131 after one week and 142 ng/dl after 4 weeks of theophylline). The clinical importance of these changes should be weighed against the potential therapeutic benefit of theophylline in individual patients.

Information for Patients:

The patient (or parent/care giver) should be instructed to seek medical advice whenever nausea, vomiting, persistent headache, insomnia or rapid heart beat occurs during treatment with theophylline, even if another cause is suspected. The patient should be instructed to contact their clinician if they develop a new illness, especially if accompanied by a persistent fever, if they experience worsening of a chronic illness, if they start or stop smoking cigarettes or marijuana, or if another clinician adds a new medication or discontinues a previously prescribed medication. Patients should be instructed to inform all clinicians involved in their care that they are taking theophylline, especially when a medication is being added or deleted from their treatment. Patients should be instructed to not alter the dose, timing of the dose, or frequency of administration without first consulting their clinician. If a dose is missed, the patient should be instructed to take the next dose at the usually scheduled time and to not attempt to make up for the missed dose.

Drug Interactions:

Theophylline interacts with a wide variety of drugs. The interaction may be pharmacodynamic, i.e., alterations in the therapeutic response to theophylline or another drug or occurrence of adverse effects without a change in serum theophylline concentration. More frequently, however, the interaction is pharmacokinetic, i.e., the rate of theophylline clearance is altered by another drug resulting in increased or decreased serum theophylline concentrations. Theophylline only rarely alters the pharmacokinetics of other drugs. The drugs listed in Table II have the potential to produce clinically significant pharmacodynamic or pharmacokinetic interactions with theophylline. The information in the “Effect” column of Table II assumes that the interacting drug is being added to a steady-state theophylline regimen. If theophylline is being initiated in a patient who is already taking a drug that inhibits theophylline clearance (e.g., cimetidine, erythromycin), the dose of theophylline required to achieve a therapeutic serum theophylline concentration will be smaller. Conversely, if theophylline is being initiated in a patient who is already taking a drug that enhances theophylline clearance (e.g., rifampin), the dose of theophylline required to achieve a therapeutic serum theophylline concentration will be larger. Discontinuation of a concomitant drug that increases theophylline clearance will result in accumulation of theophylline to potentially toxic levels, unless the theophylline dose is appropriately reduced. Discontinuation of a concomitant drug that inhibits theophylline clearance will result in decreased serum theophylline concentrations, unless the theophylline dose is appropriately increased. The drugs listed in Table III have either been documented not to interact with theophylline or do not produce a clinically significant interaction (i.e., <15% change in theophylline clearance).

The listing of drugs in Table II and III are current as of February 9, 1995. New interactions are continuously being reported for theophylline, especially with new chemical entities. The clinician should not assume that a drug does not interact with theophylline if it is not listed in Table II. Before addition of a newly available drug in a patient receiving theophylline, the package insert of the new drug and/or the medical literature should be consulted to determine if an interaction between the new drug and theophylline has been reported.

Table II. Clinically significant drug interactions with theophylline*.

Drug | Type of Interaction | Effect**
Adenosine | Theophylline blocks adenosine receptors | Higher doses of adenosine may be required to achieve desired effect
Alcohol | A single large dose of alcohol (3 ml/kg of whiskey) decreases theophylline clearance for up to 24 hours | 30% increase
Allopurinol | Decreases theophylline clearance doses >600 mg/day. | 25% increase
Amino glutethimide | Increases theophylline clearance by induction of microsomal enzyme activity. | 25% decrease
Carbamazepine | Similar to aminoglutethimide | 30% decrease
Cimetidine | Decreases theophylline clearance by inhibiting cytochrome P450 1A2 | 70% increase
Ciprofloxacin | Similar to cimetidine | 40% increase
Clarithromycin | Similar to erythromycin | 25% increase
Diazepam | Benzodiazepines increase CNS concentrations of adenosine, a potent CNS depressant, while theophylline blocks adenosine receptors | Larger diazepam doses may be required to produce desired level of sedation. Discontinuation of theophylline without reduction of diazepam dose may result in respiratory depression.
Disulfiram | Decreases theophylline clearance by inhibiting hydroxylation and demethylation | 50% increase
Enoxacin | Similar to cimetidine. | 300% increase
Ephedrine | Synergistic CNS effects. | Increased frequency of nausea, nervousness, and insomnia.
Erythromycin | Erythromycin metabolite decreases theophylline clearance by inhibiting cytochrome P450 3A3 | Erythromycin steady-state serum concentrations decrease by a similar amount
Estrogen | Estrogen containing oral contraceptives decrease theophylline clearance in a dose- dependent fashion. The effect of progesterone on theophylline clearance is unknown | 30% increase
Flurazepam | Similar to diazepam. | Similar to diazepam.
Fluvoxamine | Similar to cimetidine. | Similar to cimetidine.
Halothane | Halothane sensitizes the myocardium to catecholamines, theophylline increases release of endogenous catecholamines. | Increased risk of ventricular arrhythmias
Interferon, human recombinant alpha-A | Decreases theophylline clearance. | 100% increase
Isoproterenol (IV) | Increases theophylline clearance. | 20% decrease
Ketamine | Pharmacologic | May lower theophylline seizure threshold.
Lithium | Theophylline increases renal lithium clearance. | Lithium dose required to achieve a therapeutic serum concentration increased an average of 60%.
Lorazepam | Similar to diazepam. | Similar to diazepam.
Methotrexate (MTX) | Decreases theophylline clearance. | 20% increase after low dose MTX, higher dose MTX may have a greater effect.
Mexiletine | Similar to disulfiram. | 80% increase
Midazolam | Similar to diazepam. | Similar to diazepam.
Moricizine | Increases theophylline clearance. | 25% decrease
Pancuronium | Theophylline may antagonize non-depolarizing neuromuscular blocking effects; possibly due to phosphodiesterase inhibition. | Larger dose of pancuronium may be required to achieve neuromuscular blockade.
Pentoxifylline | Decreases theophylline clearance. | 30% increase
Phenobarbital (PB) | Similar to aminoglutethimide. | 25% decrease after two weeks of concurrent PB.
Phenytoin | Phenytoin increases theophylline clearance by increasing microsomal enzyme activity. Theophylline decreases phenytoin absorption. | Serum theophylline and phenytoin concentrations decrease about 40%.
Propafenone | Decreases theophylline clearance and pharmacologic interaction. | 40% increase. Beta-2 blocking effect may decrease efficacy of theophylline.
Propranolol | Similar to cimetidine and pharmacologic interaction. | 100% increase. Beta-2 blocking effect may decrease efficacy of theophylline.
Rifampin | Increases theophylline clearance by increasing cytochrome P450 1A2 and 3A3 activity. | 20-40% decrease
Sulfinpyrazone | Increases theophylline clearance by increasing demethylation and hydroxylation. Decreases renal clearance of theophylline. | 20% decrease
Tacrine | Similar to cimetidine, also increases renal clearance of theophylline. | 90% increase
Thiabendazole | Decreases theophylline clearance. | 190% increase
Ticlopidine | Decreases theophylline clearance. | 60% increase
Troleandomycin | Similar to erythromycin. | 33-100% increase depending on troleandomycin dose.
Verapamil | Similar to disulfiram. | 20% increase

*Refer to PRECAUTIONS, Drug Interactions for further information regarding table
**Average effect on steady state theophylline concentration or other clinical effect for pharmacologic interactions. Individual patients may experience larger changes in serum theophylline concentration than the value listed.

Table III. Drugs that have been documented not to interact with theophylline or drugs that produce no clinically significant interaction with theophylline.*

albuterol, systemic and inhaled | felodipine finasteride | Nizatidinen orfloxacin
amoxicillin | hydrocortisone | ofloxacin
ampicillin, with or without sulbactam | isoflurane isoniazid | omeprazole prednisone, prednisolone
atenolol | isradipine | ranitidine
azithromycin | influenza vaccine | rifabutin
Caffeine, dietary ingestion | ketoconazole lomefloxacin | roxithromycin sorbitol
Cefactor | mebendazole | (purgative doses do not inhibit theophylline absorption)
co-trimoxazole (trimethoprim and sulfamethoxazole) | Medroxyprogesterone methylprednisolone | (purgative doses do not inhibit theophylline absorption)
diltiazem | metronidazole | sucralfate
dirithromycin | metoprolol | terbutaline, systemic
enflurane | nadolol | terfenadine
famotidine | nifedipine | tetracycline
 |  | tocainide

*Refer to PRECAUTIONS, Drug Interactionsfor information regarding table.

The Effect of Other Drugs on Theophylline Serum Concentration Measurements:

Most serum theophylline assays in clinical use are immunoassays which are specific for theophylline. Other xanthines such as caffeine, dyphylline, and pentoxifylline are not detected by these assays. Some drugs (e.g., cefazolin, cephalothin), however, may interfere with certain HPLC techniques. Caffeine and xanthine metabolites in neonates or patients with renal dysfunction may cause the reading from some dry reagent office methods to be higher than the actual serum theophylline concentration.

Carcinogenesis, Mutagenesis, and Impairment of Fertility:

Long term carcinogenicity studies have been carried out in mice (oral doses 30-150 mg/kg) and rats (oral doses 5-75mg/kg). Results are pending.

Theophylline has been studied in Ames salmonella, in vivoand in vitrocytogenetics, micronucleus and Chinese hamster ovary test systems and has not been shown to be genotoxic.

In a 14 week continuous breeding study, theophylline, administered to mating pairs of B6C3F1 mice at oral doses of 120, 270 and 500 mg/kg (approximately 1.0-3.0 times the human dose on a mg/m^2basis) impaired fertility, as evidenced by decreases in the number of live pups per litter, decreases in the mean number of litters per fertile pair, and increases in the gestation period at the high dose as well as decreases in the proportion of pups born alive at the mid and high dose.

In 13 week toxicity studies, theophylline was administered to F344 rats and B6C3F1 mice at oral doses of 40-300 mg/kg (approximately 2.0 times the human dose on a mg/m^2basis). At the high dose, systemic toxicity was observed in both species including decreases in testicular weight.

Pregnancy:

There are no adequate and well controlled studies in pregnant women. Additionally, there are no teratogenicity studies in non-rodents (e.g., rabbits). Theophylline was not shown to be teratogenic in CD-1 mice at oral doses up to 400 mg/kg, approximately 2.0 times the human dose on a mg/m^2basis or in CD-1 rats at oral doses up to 260 mg/kg, approximately 3.0 times the recommended human dose on a mg/m^2basis. At a dose of 220 mg/kg, embryotoxicity was observed in rats in the absence of maternal toxicity.

Nursing Mothers:

Theophylline is excreted into breast milk and may cause irritability or other signs of mild toxicity in nursing human infants. The concentration of theophylline in breast milk is about equivalent to the maternal serum concentration. An infant ingesting a liter of breast milk containing 10-20 mcg/mL of theophylline per day is likely to receive 10-20 mg of theophylline per day. Serious adverse effects in the infant are unlikely unless the mother has toxic serum theophylline concentrations.

Pediatric Use:

Theophylline is safe and effective for the approved indications in pediatric patients (See INDICATIONS AND USAGE). The maintenance dose of theophylline must be selected with caution in pediatric patients since the rate of theophylline clearance is highly variable across the age range of neonates to adolescents (see CLINICAL PHARMACOLOGY, Table I, WARNINGS, and DOSAGE AND ADMINISTRATION, Table V). Due to the immaturity of theophylline metabolic pathways in infants under the age of one year, particular attention to dosage selection and frequent monitoring of serum theophylline concentrations are required when theophylline is prescribed to pediatric patients in this age group.

Geriatric Use:

Elderly patients are at significantly greater risk of experiencing serious toxicity from theophylline than younger patients due to pharmacokinetic and pharmacodynamic changes associated with aging. Theophylline clearance is reduced in patients greater than 60 years of age, resulting in increased serum theophylline concentrations in response to a given theophylline dose. Protein binding may be decreased in the elderly resulting in a larger proportion of the total serum theophylline concentration in the pharmacologically active unbound form. Elderly patients also appear to be more sensitive to the toxic effects of theophylline after chronic overdosage than younger patients. For these reasons, the maximum daily dose of theophylline in patients greater than 60 years of age ordinarily should not exceed 400 mg/day unless the patient continues to be symptomatic and the peak steady state serum theophylline concentration is <10 mcg/mL (see DOSAGE AND ADMINISTRATION). Theophylline doses greater than 400 mg/d should be prescribed with caution in elderly patients.

ADVERSE REACTIONS

Adverse reactions associated with theophylline are generally mild when peak serum theophylline concentrations are <20 mcg/ mL and mainly consist of transient caffeine-like adverse effects such as nausea, vomiting, headache, and insomnia. When peak serum theophylline concentrations exceed 20 mcg/mL, however, theophylline produces a wide range of adverse reactions including persistent vomiting, cardiac arrhythmias, and intractable seizures which can be lethal (see OVERDOSAGE). The transient caffeine-like adverse reactions occur in about 50% of patients when theophylline therapy is initiated at doses higher than recommended initial doses (e.g., >300 mg/day in adults and >12 mg/kg/day in children beyond >1 year of age). During the initiation of theophylline therapy, caffeine-like adverse effects may transiently alter patient behavior, especially in school age children, but this response rarely persists. Initiation of theophylline therapy at a low dose with subsequent slow titration to a predetermined age-related maximum dose will significantly reduce the frequency of these transient adverse effects (see DOSAGE AND ADMINISTRATION, Table V). In a small percentage of patients (<3% of children and <10% of adults) the caffeine-like adverse effects persist during maintenance therapy, even at peak serum theophylline concentrations within the therapeutic range (i.e., 10-20 mcg/mL). Dosage reduction may alleviate the caffeine-like adverse effects in these patients, however, persistent adverse effects should result in a reevaluation of the need for continued theophylline therapy and the potential therapeutic benefit of alternative treatment.

Other adverse reactions that have been reported at serum theophylline concentrations <20 mcg/mL include diarrhea, irritability, restlessness, fine skeletal muscle tremors, and transient diuresis. In patients with hypoxia secondary to COPD, multifocal atrial tachycardia and flutter have been reported at serum theophylline concentrations 15 mcg/mL. There have been a few isolated reports of seizures at serum theophylline concentrations <20 mcg/mL in patients with an underlying neurological disease or in elderly patients. The occurrence of seizures in elderly patients with serum theophylline concentrations <20 mcg/mL may be secondary to decreased protein binding resulting in a larger proportion of the total serum theophylline concentration in the pharmacologically active unbound form. The clinical characteristics of the seizures reported in patients with serum theophylline concentrations <20 mcg/mL have generally been milder than seizures associated with excessive serum theophylline concentrations resulting from an overdose (i.e., they have generally been transient, often stopped without anticonvulsant therapy, and did not result in neurological residua).

Table IV. Manifestations of theophylline toxicity.*

 | Percentage of patients reported with sign or symptom
 | Acute Overdose (Large Single Dose) |  | Chronic Overdosage (Multiple Excessive Doses)
Sign/Symptom | Study 1 (n=157) | Study 2 (n=14) | Study 1 (n=92) | Study 2 (n=102)
Asymptomatic | NR** | 0 | NR** | 6
Gastrointestinal
Vomiting | 73 | 93 | 30 | 61
Abdominal Pain | NR** | 21 | NR** | 12
Diarrhea | NR** | 0 | NR** | 14
Hematemesis | NR** | 0 | NR** | 2
Metabolic/Other
Hypokalemia | 85 | 79 | 44 | 43
Hyperglycemia | 98 | NR** | 18 | NR**
Acid/base disturbance | 34 | 21 | 9 | 5
Rhabdomyolysis | NR** | 7 | NR** | 0
Cardiovascular
Sinus tachycardia | 100 | 86 | 100 | 62
Other supraventricular tachycardias | 2 | 21 | 12 | 14
Ventricular premature beats | 3 | 21 | 10 | 19
Atrial fibrillation or flutter | 1 | NR** | 12 | NR**
Multifocal atrial tachycardia | 0 | NR** | 2 | NR**
Ventricular arrhythmias with hemodynamic instability | 7 | 14 | 40 | 0
Hypotension/shock | NR** | 21 | NR** | 8
Neurologic
Nervousness | NR** | 64 | NR** | 21
Tremors | 38 | 29 | 16 | 14
Disorientation | NR** | 7 | NR** | 11
Seizures | 5 | 14 | 14 | 5
Death | 3 | 21 | 10 | 4

*These data are derived from two studies in patients with serum theophylline concentrations >30 mcg/mL. In the first study (Study #1 - Shanon, Ann Intern Med 1993;119:1161-67), data were prospectively collected from 249 consecutive cases of theophylline toxicity referred to a regional poison center for consultation. In the second study (Study #2 - Sessler, Am J Med 1990;88:567-76), data were retrospectively collected from 116 cases with serum theophylline concentrations >30 mcg/mL among 6000 blood samples obtained for measurement of serum theophylline concentrations in three emergency departments. Differences in the incidence of manifestations of theophylline toxicity between the two studies may reflect sample selection as a result of study design (e.g., in Study #1, 48% of the patients had acute intoxications versus only 10% in Study #2) and different methods of reporting results.

**NR = Not reported in a comparable manner

OVERDOSAGE

General:

The chronicity and pattern of theophylline overdosage significantly influences clinical manifestations of toxicity, management and outcome. There are two common presentations: (1) acute overdose, i.e.,ingestion of a single large excessive dose (>10 mg/kg) as occurs in the context of an attempted suicide or isolated medication error, and (2) chronic overdosage, i.e.,ingestion of repeated doses that are excessive for the patient's rate of theophylline clearance. The most common causes of chronic theophylline overdosage include patient or care giver error in dosing, clinician prescribing of an excessive dose or a normal dose in the presence of factors known to decrease the rate of theophylline clearance, and increasing the dose in response to an exacerbation of symptoms without first measuring the serum theophylline concentration to determine whether a dose increase is safe.

Severe toxicity from theophylline overdose is a relatively rare event. In one health maintenance organization, the frequency of hospital admissions for chronic overdosage of theophylline was about 1 per 1000 person-years exposure. In another study, among 6000 blood samples obtained for measurement of serum theophylline concentration, for any reason, from patients treated in an emergency department, 7% were in the 20-30 mcg/mL range and 3% were >30 mcg/mL. Approximately two-thirds of the patients with serum theophylline concentrations in the 20-30 mcg/mL range had one or more manifestations of toxicity while >90% of patients with serum theophylline concentrations >30mcg/mL were clinically intoxicated. Similarly, in other reports, serious toxicity from theophylline is seen principally at serum concentrations >30 mcg/mL.

Several studies have described the clinical manifestations of theophylline overdose and attempted to determine the factors that predict life-threatening toxicity. In general, patients who experience an acute overdose are less likely to experience seizures than patients who have experienced a chronic overdosage, unless the peak serum theophylline concentration is >100 mcg/mL. After a chronic overdosage, generalized seizures, life-threatening cardiac arrhythmias, and death may occur at serum theophylline concentrations >30 mcg/mL. The severity of toxicity after chronic overdosage is more strongly correlated with the patient's age than the peak serum theophylline concentration; patients >60 years are at the greatest risk for severe toxicity and mortality after a chronic overdosage. Pre-existing or concurrent disease may also significantly increase the susceptibility of a patient to a particular toxic manifestation, e.g., patients with neurologic disorders have an increased risk of seizures and patients with cardiac disease have an increased risk of cardiac arrhythmias for a given serum theophylline concentration compared to patients without the underlying disease.

The frequency of various reported manifestations of theophylline overdose according to the mode of overdose are listed in Table IV. Other manifestations of theophylline toxicity include increases in serum calcium, creatine kinase, myoglobin and leukocyte count, decreases in serum phosphate and magnesium, acute myocardial infarction, and urinary retention in men with obstructive uropathy. Seizures associated with serum theophylline concentrations >30 mcg/mL are often resistant to anticonvulsant therapy and may result in irreversible brain injury if not rapidly controlled. Death from theophylline toxicity is most often secondary to cardiorespiratory arrest and/or hypoxic encephalopathy following prolonged generalized seizures or intractable cardiac arrhythmias causing hemodynamic compromise.

Overdose Management:

General Recommendations for Patients with Symptoms of Theophylline Overdose or Serum Theophylline Concentrations >30 mcg/mL (Note: Serum theophylline concentrations may continue to increase after presentation of the patient for medical care.)

1. While simultaneously instituting treatment, contact a regional poison center to obtain updated information and advice on individualizing the recommendations that follow.

2. Institute supportive care, including establishment of intravenous access, maintenance of the airway, and electrocardiographic monitoring.

3. Treatment of seizuresBecause of the high morbidity and mortality associated with theophylline-induced seizures, treatment should be rapid and aggressive. Anticonvulsant therapy should be initiated with an intravenous benzodiazepine, e.g., diazepam, in increments of 0.1-0.2 mg/kg every 1-3 minutes until seizures are terminated. Repetitive seizures should be treated with a loading dose of phenobarbital (20 mg/kg infused over 30-60 minutes). Case reports of theophylline overdose in humans and animal studies suggest that phenytoin is ineffective in terminating theophylline-induced seizures. The doses of benzodiazepines and phenobarbital required to terminate theophylline-induced seizures are close to the doses that may cause severe respiratory depression or respiratory arrest; the clinician should therefore be prepared to provide assisted ventilation. Elderly patients and patients with COPD may be more susceptible to the respiratory depressant effects of anticonvulsants. Barbiturate-induced coma or administration of general anesthesia may be required to terminate repetitive seizures or status epilepticus. General anesthesia should be used with caution in patients with theophylline overdose because fluorinated volatile anesthetics may sensitize the myocardium to endogenous catecholamines released by theophylline. Enflurane appears to less likely to be associated with this effect than halothane and may, therefore, be safer. Neuromuscular blocking agents alone should not be used to terminate seizures since they abolish the musculoskeletal manifestations without terminating seizure activity in the brain.

4. Anticipate Need for AnticonvulsantsIn patients with theophylline overdose who are at high risk for theophylline-induced seizures, e.g., patients with acute overdoses and serum theophylline concentrations >100 mcg/mL chronic overdosage in patients >60 years of age with serum theophylline concentrations >30 mcg/mL, the need for anticonvulsant therapy should be anticipated. A benzodiazepine such as diazepam should be drawn into a syringe and kept at the patient's bedside and medical personnel qualified to treat seizures should be immediately available. In selected patients at high risk for theophylline-induced seizures, consideration should be given to the administration of prophylactic anticonvulsant therapy. Situations where prophylactic anticonvulsant therapy should be considered in high risk patients include anticipated delays in instituting methods for extracorporeal removal of theophylline (e.g., transfer of a high risk patient from one health care facility to another for extracorporeal removal) and clinical circumstances that significantly interfere with efforts to enhance theophylline clearance (e.g., a neonate where dialysis may not be technically feasible or a patient with vomiting unresponsive to antiemetics who is unable to tolerate multiple-dose oral activated charcoal). In animal studies, prophylactic administration of phenobarbital, but not phenytoin,has been shown to delay the onset of theophylline induced generalized seizures and to increase the dose of theophylline required to induce seizures (i.e., markedly increases the LD50). Although there are no controlled studies in humans, a loading dose of intravenous Phenobarbital (20 mg/kg infused over 60 minutes) may delay or prevent life-threatening seizures in high risk patients while efforts to enhance theophylline clearance are continued. Phenobarbital may cause respiratory depression, particularly in elderly patients and patients with COPD.

5. Treatment of cardiac arrhythmiasSinus tachycardia and simple ventricular premature beats are not harbingers of life-threatening arrhythmias, they do not require treatment in the absence of hemodynamic compromise, and they resolve with declining serum theophylline concentrations. Other arrhythmias, especially those associated with hemodynamic compromise, should be treated with antiarrhythmic therapy appropriate for the type of arrhythmia.

6. Gastrointestinal decontaminationOral activated charcoal (0.5 g/kg up to 20 g and repeat at least once 1-2 hours after the first dose) is extremely effective in blocking the absorption of theophylline throughout the gastrointestinal tract, even when administered several hours after ingestion. If the patient is vomiting, the charcoal should be administered through a nasogastric tube or after administration of an antiemetic. Phenothiazine antiemetics such as prochlorperazine or perphenazine should be avoided since they can lower the seizure threshold and frequently cause dystonic reactions. A single dose of sorbitol may be used to promote stooling to facilitate removal of theophylline bound to charcoal from the gastrointestinal tract. Sorbitol, however, should be dosed with caution since it is a potent purgative which can cause profound fluid and electrolyte abnormalities, particularly after multiple doses. Commercially available fixed combinations of liquid charcoal and sorbitol should be avoided in young children and after the first dose in adolescents and adults since they do not allow for individualization of charcoal and sorbitol dosing. Ipecac syrup should be avoided in theophylline overdoses. Although ipecac induces emesis, it does not reduce the absorption of theophylline unless administered within 5 minutes of ingestion and even then is less effective than oral activated charcoal. Moreover, ipecac induced emesis may persist for several hours after a single dose and significantly decrease the retention and the effectiveness of oral activated charcoal.

7. Serum Theophylline Concentration MonitoringThe serum theophylline concentration should be measured immediately upon presentation, 2-4 hours later, and then at sufficient intervals, e.g., every 4 hours, to guide treatment decisions and to assess the effectiveness of therapy. Serum theophylline concentrations may continue to increase after presentation of the patient for medical care as a result of continued absorption of theophylline from the gastrointestinal tract. Serial monitoring of serum theophylline serum concentrations should be continued until it is clear that the concentration is no longer rising and has returned to non-toxic levels.

8. General Monitoring ProceduresElectrocardiographic monitoring should be initiated on presentation and continued until the serum theophylline level has returned to a non-toxic level. Serum electrolytes and glucose should be measured on presentation and at appropriate intervals indicated by clinical circumstances. Fluid and electrolyte abnormalities should be promptly corrected. Monitoring and treatment should be continued until the serum concentration decreases below 20 mcg/mL.

9. Enhance clearance of theophyllineMultiple-dose oral activated charcoal (e.g., 0.5 mg/kg up to 20 g, every two hours) increases the clearance of theophylline at least twofold by adsorption of theophylline secreted into gastrointestinal fluids. Charcoal must be retained in, and pass through, the gastrointestinal tract to be effective; emesis should therefore be controlled by administration of appropriate antiemetics. Alternatively, the charcoal can be administered continuously through a nasogastric tube in conjunction with appropriate antiemetics. A single dose of sorbitol may be administered with the activated charcoal to promote stooling to facilitate clearance of the adsorbed theophylline from the gastrointestinal tract. Sorbitol alone does not enhance clearance of theophylline and should be dosed with caution to prevent excessive stooling which can result in severe fluid and electrolyte imbalances. Commercially available fixed combinations of liquid charcoal and sorbitol should be avoided in young children and after the first dose in adolescents and adults since they do not allow for individualization of charcoal and sorbitol dosing. In patients with intractable vomiting, extracorporeal methods of theophylline removal should be instituted (see OVERDOSAGE, Extracorporeal Removal).

Specific Recommendations:

Acute Overdose

A. Serum Concentration >20<30 mcg/mL

1. Administer a single dose of oral activated charcoal.
2. Monitor the patient and obtain a serum theophylline concentration in 2-4 hours to insure that the
concentration is not increasing.
B. Serum Concentration >30<100 mcg/mL
1. Administer multiple dose oral activated charcoal and measures to control emesis.
2. Monitor the patient and obtain serial theophylline concentrations every 2-4 hours to gauge the
effectiveness of therapy and to guide further treatment decisions.
3. Institute extracorporeal removal if emesis, seizures, or cardiac arrhythmias cannot be adequately
controlled (see OVERDOSAGE, Extracorporeal Removal).
C. Serum Concentration >100 mcg/mL
1. Consider prophylactic anticonvulsant therapy.
2. Administer multiple-dose oral activated charcoal and measures to control emesis.
3. Consider extracorporeal removal, even if the patient has not experienced a seizure (see OVERDOSAGE, Extracorporeal Removal).
4. Monitor the patient and obtain serial theophylline concentrations every 2-4 hours to gauge the
effectiveness of therapy and to guide further treatment decisions.
Chronic Overdosage
A. Serum Concentration >20<30 mcg/mL (with manifestations of theophylline toxicity)
1. Administer a single dose of oral activated charcoal.
2. Monitor the patient and obtain a serum theophylline concentration in 2-4 hours to insure that the
concentration is not increasing.
B. Serum Concentration >30 mcg/mL in patients <60 years of age
1. Administer multiple-dose oral activated charcoal and measures to control emesis.
2. Monitor the patient and obtain serial theophylline concentrations every 2-4 hours to gauge the
effectiveness of therapy and to guide further treatment decisions.
3. Institute extracorporeal removal if emesis, seizures, or cardiac arrhythmias cannot be adequately
controlled (see OVERDOSAGE, Extracorporeal Removal).
C. Serum Concentration >30 mcg/mL in patients ≥60 years of age.
1. Consider prophylactic anticonvulsant therapy.
2. Administer multiple-dose oral activated charcoal and measures to control emesis.
3. Consider extracorporeal removal even if the patient has not experienced a seizure (see OVERDOSAGE, Extracorporeal Removal).
4. Monitor the patient and obtain serial theophylline concentrations every 2-4 hours to gauge the
effectiveness of therapy and to guide further treatment decisions.

Extracorporeal Removal:

Increasing the rate of theophylline clearance by extracorporeal methods may rapidly decrease serum concentrations, but the risks of the procedure must be weighed against the potential benefit. Charcoal hemoperfusion is the most effective method of extracorporeal removal, increasing theophylline clearance up to six fold, but serious complications, including hypotension, hypocalcemia, platelet consumption and bleeding diatheses may occur. Hemodialysis is about as efficient as multiple-dose oral activated charcoal and has a lower risk of serious complications than charcoal hemoperfusion. Hemodialysis should be considered as an alternative when charcoal hemoperfusion is not feasible and multiple-dose oral charcoal is ineffective because of intractable emesis. Serum theophylline concentrations may rebound 5-10 mcg/mL after discontinuation of charcoal hemoperfusion or hemodialysis due to redistribution of theophylline from the tissue compartment. Peritoneal dialysis is ineffective for theophylline removal; exchange transfusions in neonates have been minimally effective.

DOSAGE AND ADMINISTRATION

General Considerations:

The steady-state peak serum theophylline concentration is a function of the dose, the dosing interval, and the rate of theophylline absorption and clearance in the individual patient. Because of marked individual differences in the rate of theophylline clearance, the dose required to achieve a peak serum theophylline concentration in the 10-20 mcg/mL range varies fourfold among otherwise similar patients in the absence of factors known to alter theophylline clearance (e.g., 400- 1600 mg/day in adults <60 years old and 10-36 mg/kg/day in children 1-9 years old). For a given population there is no single theophylline dose that will provide both safe and effective serum concentrations for all patients. Administration of the median theophylline dose required to achieve a therapeutic serum theophylline concentration in a given population may result in either sub-therapeutic or potentially toxic serum theophylline concentrations in individual patients. For example, at a dose of 900 mg/d in adults <60 years or 22 mg/kg/d in children 1-9 years, the steady state peak serum theophylline concentration will be <10 mcg/mL in about 30% of patients, 10-20 mcg/mL in about 50% and 20-30 mcg/mL in about 20% of patients. The dose of theophylline must be individualized on the basis of peak serum theophylline concentration measurements in order to achieve a dose that will provide maximum potential benefit with minimal risk to adverse effects.

Transient caffeine-like adverse effects and excessive serum concentrations in slow metabolizers can be avoided in most patients by starting with a sufficiently low dose and slowly increasing the dose, if judged to be clinically indicated, in small increments (See Table V). Dose increases should only be made if the previous dosage is well tolerated and at intervals of no less than 3 days to allow serum theophylline concentrations to reach the new steady state. Dosage adjustment should be guided by serum theophylline concentration measurement (see PRECAUTIONS, Laboratory Testsand DOSAGE AND ADMINISTRATION, Table VI). Health care providers should instruct patients and care givers to discontinue any dosage that causes adverse effects, to withhold the medication until these symptoms are gone and to then resume therapy at a lower, previously tolerated dosage (see WARNINGS).

If the patient's symptoms are well controlled, there are no apparent adverse effects, and no intervening factors that might alter dosage requirements (see WARNINGSand PRECAUTIONS), serum theophylline concentrations should be monitored at 6 month intervals for rapidly growing children and at yearly intervals for all others. In acutely ill patients, serum theophylline concentrations should be monitored at frequent intervals, e.g., every 24 hours.

Theophylline distributes poorly into body fat, therefore, mg/kg dose should be calculated on the basis of ideal body weight.

Table V contains theophylline dosing titration schema recommended for patients in various age groups and clinical circumstances. Table VI contains recommendations for theophylline dosage adjustment based upon serum theophylline concentrations. Application of these general dosing recommendations to individual patients must take into account the unique clinical characteristics of each patient. In general, these recommendations should serve as the upper limit for dosage adjustments in order to decrease the risk of potentially serious adverse events associated with unexpected large increases in serum theophylline concentration.

Table V. Dosing initiation and titration (as anhydrous theophylline).*

A. Infants <1 year old.

1. Initial Dosage

a. Premature Neonates:

i.< 24 days postnatal age; 1.0 mg/kg every 12 hr

ii.≥ 24 days postnatal age; 1.5 mg/kg every 12 hr

b. Full term infants and infants up to 52 weeks of age:

Total daily dose (mg) = [(0.2 x age in weeks)+5.0] x (Kg body Wt).

i.up to age 26 weeks; divide dose into 3 equal amounts administered at 8 hour intervals.

ii.≥26 weeks of age; divide dose into 4 equal amounts administered at 6 hour intervals.

2. Final Dosage.Adjusted to maintain a peak steady state serum theophylline concentration of 5-10 mcg/ml in neonates and 10-15 mcg/mL in older infants (see TableVI). Since the time required to reach steady state is a function of theophylline half-life, up to 5 days may be required to achieve steady state in a premature neonate, while only 2-3 days may be required in a 6 month old infant without other risk factors for impaired clearance in the absence of a loading dose. If a serum theophylline concentration is obtained before steady state is achieved, the maintenance dose should not be increased, even if the serum theophylline concentration is <10 mcg/mL.

B. Children (1-15 years) and adults (16-60 years) without risk factors for impaired clearance.

Titration Step | Children < 45 Kg | Children > 45 Kg and Adults
1. Starting Dosage | 12-14 mg/kg/day up to a maximum of 300 mg/day divided Q4-6 hrs* | 300 mg/day divided Q6-8 hrs*
2. After 3 days, if tolerated, increase dose to: | 16 mg/kg/day up to a maximum of 400 mg/day divided Q4-6 hrs* | 400 mg/day divided Q6-8 hrs*
3. After 3 more days, if tolerated dose to: | 20 mg/kg/day increase up to a maximum of 600 mg/day divided Q4-6 hrs* | 600 mg/day divided Q6-8 hrs*

C. Patients With Risk Factors For Impaired Clearance, The Elderly (>60 Years), And Those In WhomIt Is Not Feasible To Monitor Serum Theophylline Concentrations:

In children 1-15 years of age, the final theophylline dose should not exceed 16 mg/kg/day up to a maximum of 400 mg/day in the presence of risk factors for reduced theophylline clearance (see WARNINGS) or if it is not feasible to monitor serum theophylline concentrations.

In adolescents 16 years and adults, including the elderly, the final theophylline dose should not exceed 400 mg/day in the presence of risk factors for reduced theophylline clearance (see WARNINGS) or if it is not feasible to monitor serum theophylline concentrations.

D. Loading Dose for Acute Bronchodilatation:

An inhaled beta-2 selective agonist, alone or in combination with a systemically administered corticosteroid, is the most effective treatment for acute exacerbations of reversible airways obstruction. Theophylline is a relatively weak bronchodilator, is less effective than an inhaled beta-2 selective agonist and provides no added benefit in the treatment of acute bronchospasm. If an inhaled or parenteral beta agonist is not available, a loading dose of an oral immediate release theophylline can be used as a temporary measure. A single 5 mg/kg dose of theophylline, in a patient who has not received any theophylline in the previous 24 hours, will produce an average peak serum theophylline concentration of 10 mcg/mL (range 5-15 mcg/mL). If dosing with theophylline is to be continued beyond the loading dose, the guidelines in Sections A.1.b., B.3, or C., above, should be utilized and serum theophylline concentration monitored at 24 hour intervals to adjust final dosage.

* Patients with more rapid metabolism, clinically identified by higher than average dose requirements, should receive a smaller dose more frequently to prevent breakthrough symptoms resulting from low trough concentrations before the next dose. A reliably absorbed slow-release formulation will decrease fluctuations and permit longer dosing intervals.

Table VI. Dosage adjustment guided by serum theophylline concentration.
Peak Serum Concentration | Dosage Adjustment
<9.9 mcg/mL | If symptoms are not controlled and current dosage is tolerated, increase dose about 25%. Recheck serum concentration after three days for further dosage adjustment
10 - 14.9 mcg/mL | If symptoms are controlled and current dosage is tolerated, maintain dose and recheck serum concentration at 6-12 month intervals. If symptoms are not controlled and current dosage is tolerated consider adding additional medication(s) to treatment regimen.
15 - 19.9 mcg/mL | Consider 10% decrease in dose to provide greater margin of safety even if current dosage is tolerated.
20 - 24.9 mcg/mL | Decrease dose by 25% even if no adverse effects are present. Recheck serum concentration after 3 days to guide further dosage adjustment.
25 - 30 mcg/mL | Skip next dose and decrease subsequent doses at least 25% even if no adverse effects are present. Recheck serum concentration after 3 days to guide further dosage adjustment. If symptomatic, consider whether overdose treatment is indicated (see recommendations for chronic overdosage).
>30 mcg/mL | Treat overdose as indicated (see recommendations for chronic overdosage). If theophylline is subsequently resumed, decrease dose by at least 50% and recheck serum concentration after 3 days to guide further dosage adjustment.

Dose reduction and/or serum theophylline concentration measurement is indicated whenever adverse effects are present, physiologic abnormalities that can reduce theophylline clearance occur (e.g., sustained fever), or a drug that interacts with theophylline is added or discontinued (see WARNINGS).

HOW SUPPLIED

Theophylline Oral Solution, USP is a clear red solution with a fruit flavor. Each tablespoonful (15 mL) contains 80 mg theophylline anhydrous.

Theophylline Oral Solution, USP is available in bottles of 473 mL (16 fl oz) NDC 62135-556-47, 15 mL Unit Dose Cup NDC 62135-556-51 and 20 Unit Dose Cups of 15 mL each NDC 62135-556-24.

RECOMMENDED STORAGE
Store at 20° to 25°C (68° to 77°); [see USP Controlled Room Temperature].
Dispense in tight container.

Manufactured for:

Chartwell RX, LLC.

Congers, NY 10920

Rev. 01/2026

L71058

PACKAGE LABEL.PRINCIPAL DISPLAY PANEL

Theophylline Oral Solution, USP 80 mg/15 mL - NDC 62135-556-47 - 473 mL Bottle Label

Theophylline Oral Solution, USP 80 mg/15 mL - NDC 62135-556-51 - 15 mL Unit Dose Cup Label